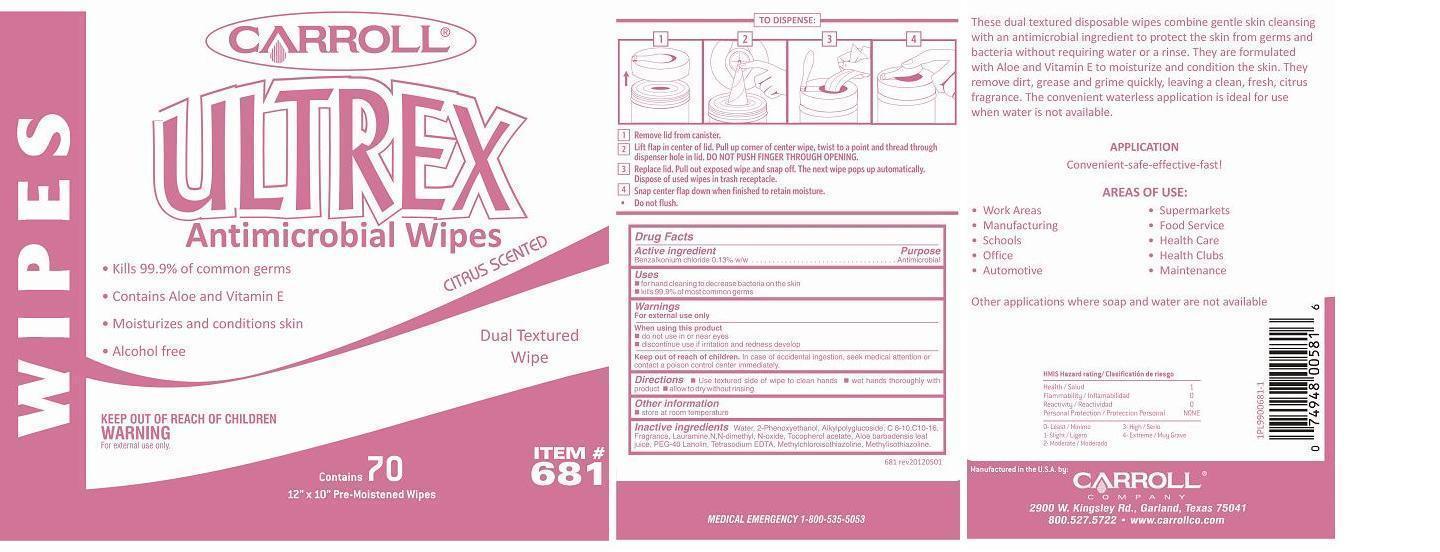 DRUG LABEL: Carroll Ultrex Antimicrobial Wipes
NDC: 10685-681 | Form: CLOTH
Manufacturer: Carroll Company
Category: otc | Type: HUMAN OTC DRUG LABEL
Date: 20180131

ACTIVE INGREDIENTS: BENZALKONIUM CHLORIDE 0.01417 g/1 1
INACTIVE INGREDIENTS: WATER; PHENOXYETHANOL; DECYL GLUCOSIDE; LAURAMINE OXIDE; .ALPHA.-TOCOPHEROL ACETATE; ALOE VERA LEAF; EDETATE SODIUM; METHYLCHLOROISOTHIAZOLINONE; METHYLISOTHIAZOLINONE

Carroll® Ultrex Antimicrobial Wipes

Drug Facts

Active ingredient

Benzalkonium chloride 0.13% w/w

Purpose

Antimicrobial

Uses

- for hand cleaning to decrease bacteria on the skin
- kills 99.9% of most common germs

Warnings

For external use only

When using this product

- do not use in or near eyes
- discontinue use if irritation and redness develop

Keep out of reach of children. In case of accidental ingestion, seek medical attention or contact a poison control center immediately.

Directions

- Use textured side of wipe to clean hands
- wet hands thoroughly with product
- allow to dry without rinsing

Other information

- store at room temperature

Inactive ingredients

Water, 2-Phenoxyethanol, Alkylpolyglucoside, C 8-10,C10-16, Fragrance, Lauramine,N,N-dimethyl, N-oxide, Tocopherol acetate, Aloe barbadensis leaf juice, PEG-40 Lanolin, Tetrasodium EDTA, Methylchloroisothiazoline, Methylisothiazoline.

Manufactured in the U.S.A. by:
CARROLL ® COMPANY
2900 W. Kingsley Rd., Garland, Texas 75041